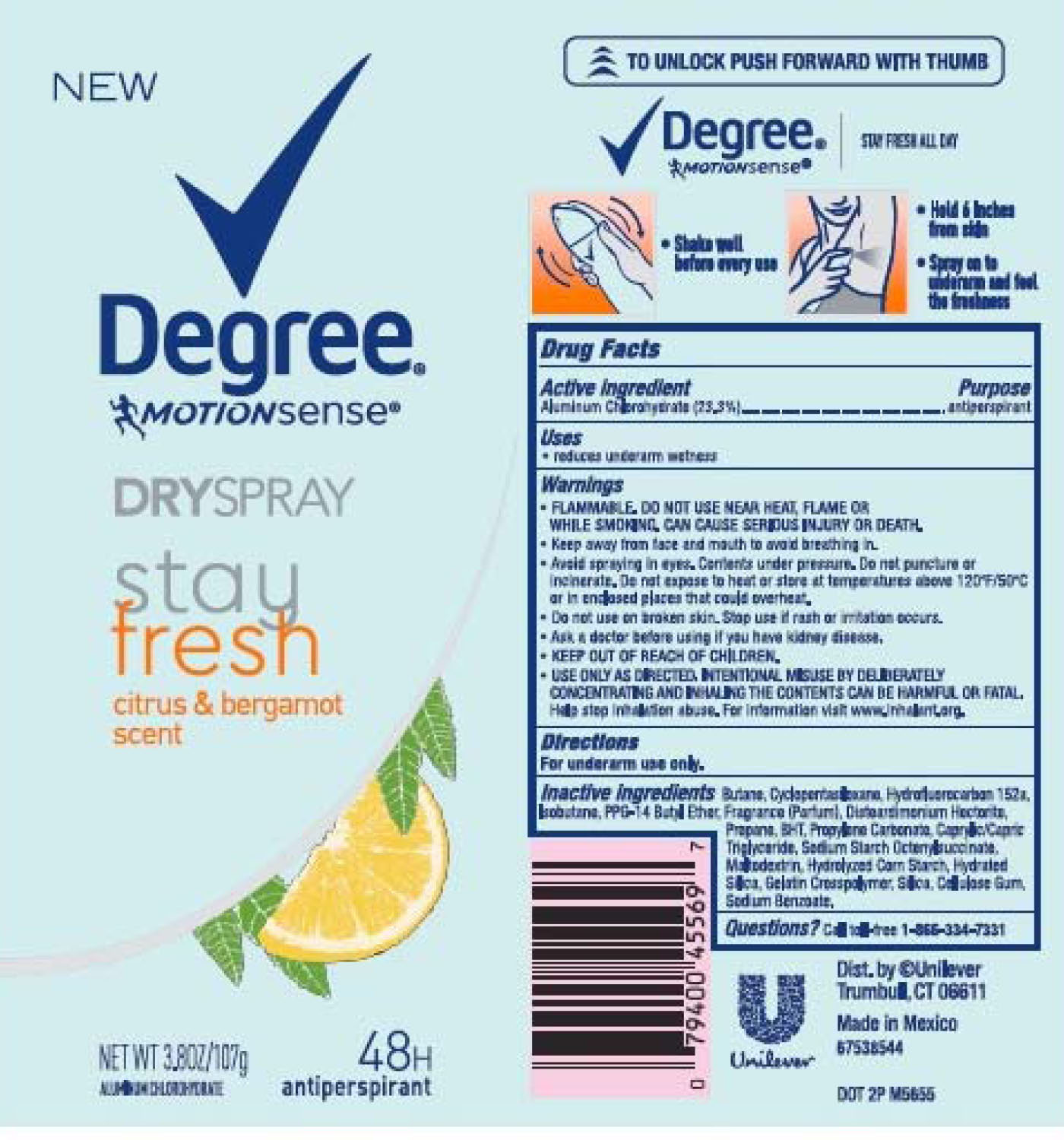 DRUG LABEL: Degree
NDC: 64942-1601 | Form: AEROSOL, SPRAY
Manufacturer: Conopco Inc. d/b/a Unilever
Category: otc | Type: HUMAN OTC DRUG LABEL
Date: 20221207

ACTIVE INGREDIENTS: ALUMINUM CHLOROHYDRATE 23.3 g/100 g
INACTIVE INGREDIENTS: MALTODEXTRIN; SILICON DIOXIDE; CARBOXYMETHYLCELLULOSE SODIUM, UNSPECIFIED FORM; SODIUM BENZOATE; BUTANE; 1,1-DIFLUOROETHANE; CYCLOMETHICONE 5; ISOBUTANE; DISTEARDIMONIUM HECTORITE; PROPANE; PROPYLENE CARBONATE; HYDRATED SILICA; STARCH, CORN; PPG-14 BUTYL ETHER; BUTYLATED HYDROXYTOLUENE; MEDIUM-CHAIN TRIGLYCERIDES

Degree MotionSense Citrus and Bergamot Scent Dry Spray 48H Antiperspirant

DEGREE MOTIONSENSE CITRUS AND BERGAMOT SCENT DRY SPRAY ANTIPERSPIRANT - aluminum chlorohydrate aerosol, spray

Degree MotionSense Citrus and Bergamot Scent Dry Spray Antiperspirant

Drug Facts

Active Ingredient:

Aluminum Chlorohydrate (23.3%)

Purpose:

antiperspirant

Uses

reduces underarm wetness

Warnings

• FLAMMABLE UNTILFULLY DRY. DO NOT USE NEAR HEAT, FLAME, OR WHILE SMOKING. CAN CAUSE SERIOUS INJURY OR DEATH.
• Keep away from face and mouth to avoid breathing in.
• Avoid spraying in eyes. Contents under pressure. Do not puncture or incinerate. Do not expose to heat or store at temperatures above 120°F/50°C or in enclosed places that could overheat.
• Do not use on broken skin. Stop use if rash or irritation occurs.
• Ask a doctor before using if you have kidney disease.
• USE ONLY AS DIRECTED. INTENTIONAL MISUSE BY DELIBERATELY CONCENTRATING AND INHALING THE CONTENTS CAN BE HARMFUL OR FATAL.
Help stop inhalation abuse. For information visit www.inhalant.org

• KEEP OUT OF REACH OF CHILDREN

Directions

For underarm use only

Inactive ingredients

Butane, Cyclopentasiloxane, Hydrofluorocarbon 152a, Isobutane, PPG-14 Butyl Ether, Fragrance (Parfum),Disteardimonium Hectorite, Propane, BHT, Propylene Carbonate, Caprylic/Capric Triglyceride, Sodium Starch Octenylsuccinate, Maltodextrin, Hydrolyzed Corn Starch, Hydrated Silica, Gelatin Crosspolymer, Silica, Cellulose Gum, Sodium Benzoate.

Questions?

Call toll-free 1-866-334-7331